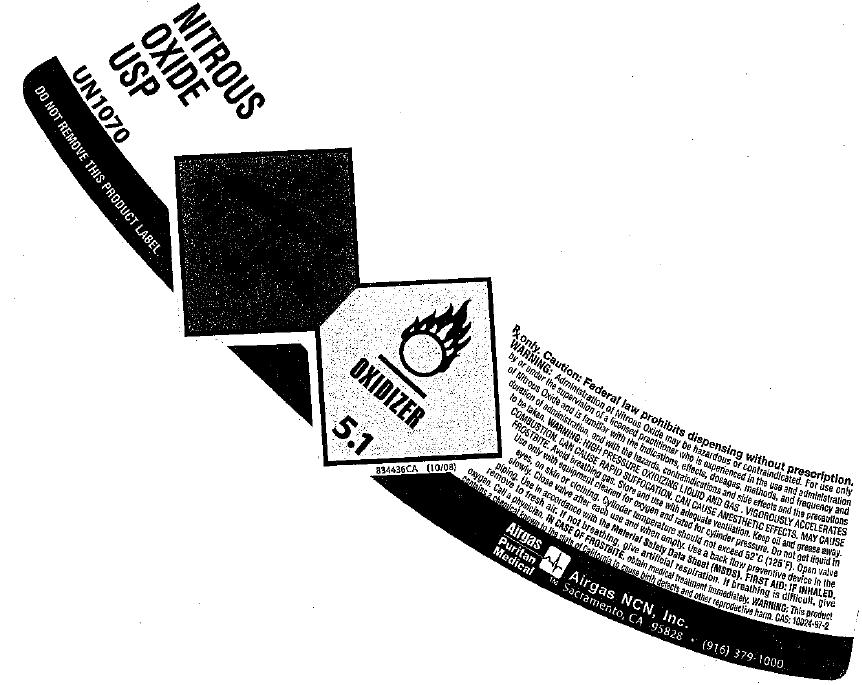 DRUG LABEL: Nitrous Oxide
NDC: 58789-006 | Form: GAS
Manufacturer: Airgas Northern California and Nevada, Inc.
Category: prescription | Type: HUMAN PRESCRIPTION DRUG LABEL
Date: 20100430

ACTIVE INGREDIENTS: Nitrous Oxide 992 mL/1 L

nitrous oxide

PACKAGE LABEL

NITROUS OXIDE USP
UN 1070 DO NOT REMOVE THIS PRODUCT LABEL.
Rx Only: Caution: Federal law prohibits dispensing without prescription. WARNING: Administration of Nitrous Oxide may hazardous or contraindicated. For use only by or under the supervision of a licensed practitioner who is experienced in the administration of Nitrous Oxide and is familiar with the indications, effects, dosages, methods, and frequency and duration of administration, and with the hazards, and contraindications, and side effects, and the precautions to be taken.
CAUTION: HIGH PRESSURE OXYDIZING LIQUID AND GAS. VIGOROUSLY ACCELERATES COMBUSTION. CAN CAUSE RAPID SUFFOCATION. CAN CAUSE ANESTHETIC EFFECTS. MAY CAUSE FROST BITE. Avoid breathing gas. Store and use with adequate ventilation. Keep oil and grease away. Use only with equipment cleaned for oxygen and rated for cylinder pressure. Do not get liquid in eyes, on skin or clothing. Cylinder temperature should not exceed 52 C(125F). Open valve slowly. Close valve after each use and when empty. Use a back flow preventive device in the piping. Use in accordance with the Material Safety Data Sheet (MSDS). FIRST AID: IF INHALED, remove to fresh air. If not breathing, give artificial respiration. If breathing is difficult, give oxygen. Call a physician. . IN CASE OF FROSTBITE obtain medical treatment immediately. WARNING: This product contains a chemical known to the state of California to cause birth defects and other reproductive harm. CAS 10024-97-2
Airgas Puritan Medical Airgas NCN, Inc. Sacramento, CA 95828 (916) 379-1000
834436CA (10/08)
Oxidizer 5.1